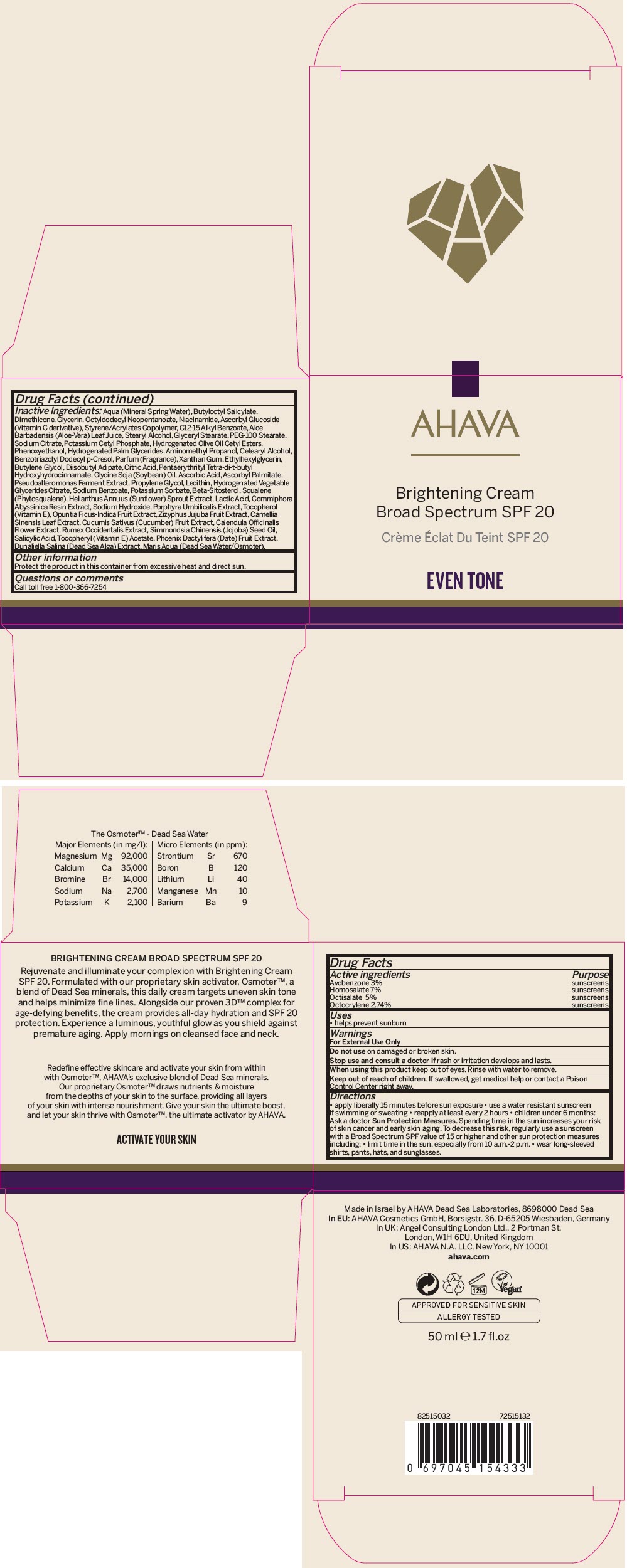 DRUG LABEL: AHAVA 
NDC: 60289-303 | Form: CREAM
Manufacturer: AHAVA - Dead Sea Laboratories Ltd
Category: otc | Type: HUMAN OTC DRUG LABEL
Date: 20241210

ACTIVE INGREDIENTS: Avobenzone 30 mg/1 mL; Homosalate 70 mg/1 mL; Octisalate 50 mg/1 mL; Octocrylene 27.4 mg/1 mL
INACTIVE INGREDIENTS: Water; Butyloctyl Salicylate; Dimethicone; Glycerin; Octyldodecyl Neopentanoate; Niacinamide; Ascorbyl Glucoside; Alkyl (C12-15) Benzoate; Aloe Vera Leaf; Stearyl Alcohol; Glyceryl Monostearate; PEG-100 Monostearate; Sodium Citrate, Unspecified Form; Potassium Cetyl Phosphate; Hydrogenated Olive Oil Cetyl Esters; Phenoxyethanol; Hydrogenated Palm Glycerides; Aminomethylpropanol; Cetostearyl Alcohol; Benzotriazolyl Dodecyl p-Cresol; Xanthan Gum; Ethylhexylglycerin; Butylene Glycol; Diisobutyl Adipate; Citric Acid Monohydrate; Pentaerythritol Tetrakis(3-(3,5-Di-Tert-Butyl-4-Hydroxyphenyl)Propionate); Soybean Oil; Ascorbic Acid; Ascorbyl Palmitate; Propylene Glycol; Sodium Benzoate; Potassium Sorbate; .Beta.-Sitosterol; Squalene; Helianthus Annuus Sprout; Lactic Acid, Unspecified Form; Commiphora Madagascariensis Resin; Sodium Hydroxide; Porphyra Umbilicalis; .Alpha.-tocopherol; Prickly Pear Fruit; Jujube Fruit; Green Tea Leaf; Cucumber; Calendula Officinalis Flower; Jojoba Oil; Salicylic Acid; .Alpha.-tocopherol acetate; Dunaliella Salina; Date

AHAVA
Brightening Broad Spectrum SPF 20

Drug Facts

ACTIVE INGREDIENT

Active ingredients | Purpose
Avobenzone 3% | sunscreens
Homosalate 7% | sunscreens
Octisalate 5% | sunscreens
Octocrylene 2.74% | sunscreens

Uses

- helps prevent sunburn

Warnings

For External Use Only

Do not use on damaged or broken skin.

Stop use and consult a doctor if rash or irritation develops and lasts.

When using this product keep out of eyes. Rinse with water to remove.

Keep out of reach of children. If swallowed, get medical help or contact a Poison Control Center right away.

Directions

- apply liberally 15 minutes before sun exposure
- use a water resistant sunscreen if swimming or sweating
- reapply at least every 2 hours
- children under 6 months: Ask a doctor

Sun Protection Measures

Spending time in the sun increases your risk of skin cancer and early skin aging. To decrease this risk, regularly use a sunscreen with a Broad Spectrum SPF value of 15 or higher and other sun protection measures including:

- limit time in the sun, especially from 10 a.m.-2 p.m.
- wear long-sleeved shirts, pants, hats, and sunglasses.

Inactive Ingredients

Aqua (Mineral Spring Water), Butyloctyl Salicylate, Dimethicone, Glycerin, Octyldodecyl Neopentanoate, Niacinamide, Ascorbyl Glucoside (Vitamin C derivative), Styrene/Acrylates Copolymer, C12-15 Alkyl Benzoate, Aloe Barbadensis (Aloe-Vera) Leaf Juice, Stearyl Alcohol, Glyceryl Stearate, PEG-100 Stearate, Sodium Citrate, Potassium Cetyl Phosphate, Hydrogenated Olive Oil Cetyl Esters, Phenoxyethanol, Hydrogenated Palm Glycerides, Aminomethyl Propanol, Cetearyl Alcohol, Benzotriazolyl Dodecyl p-Cresol, Parfum (Fragrance), Xanthan Gum, Ethylhexylglycerin, Butylene Glycol, Diisobutyl Adipate, Citric Acid, Pentaerythrityl Tetra-di-t-butyl Hydroxyhydrocinnamate, Glycine Soja (Soybean) Oil, Ascorbic Acid, Ascorbyl Palmitate, Pseudoalteromonas Ferment Extract, Propylene Glycol, Lecithin, Hydrogenated Vegetable Glycerides Citrate, Sodium Benzoate, Potassium Sorbate, Beta-Sitosterol, Squalene (Phytosqualene), Helianthus Annuus (Sunflower) Sprout Extract, Lactic Acid, Commiphora Abyssinica Resin Extract, Sodium Hydroxide, Porphyra Umbilicalis Extract, Tocopherol (Vitamin E), Opuntia Ficus-Indica Fruit Extract, Zizyphus Jujuba Fruit Extract, Camellia Sinensis Leaf Extract, Cucumis Sativus (Cucumber) Fruit Extract, Calendula Officinalis Flower Extract, Rumex Occidentalis Extract, Simmondsia Chinensis (Jojoba) Seed Oil, Salicylic Acid, Tocopheryl (Vitamin E) Acetate, Phoenix Dactylifera (Date) Fruit Extract, Dunaliella Salina (Dead Sea Alga) Extract, Maris Aqua (Dead Sea Water/Osmoter).

Other information

Protect the product in this container from excessive heat and direct sun.

Questions or comments

Call toll free 1-800-366-7254

PRINCIPAL DISPLAY PANEL - 50 ml Jar Carton

AHAVA

Brightening Cream
Broad Spectrum SPF 20

EVEN TONE